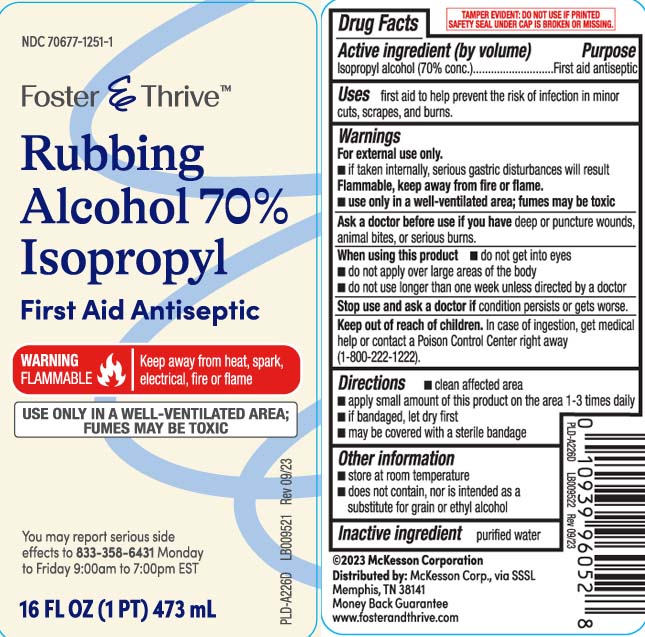 DRUG LABEL: Isopropyl alcohol
NDC: 70677-1251 | Form: LIQUID
Manufacturer: Strategic Sourcing Services LLC
Category: otc | Type: HUMAN OTC DRUG LABEL
Date: 20250414

ACTIVE INGREDIENTS: ISOPROPYL ALCOHOL 70 mL/100 mL
INACTIVE INGREDIENTS: WATER

Drug Facts

Active ingredient (by volume)

Isopropyl alcohol (70% conc.)

Purpose

First aid antiseptic

Uses

first aid to help prevent the risk of infection in minor cuts, scrapes, and burns.

Warnings

For external use only.

- If taken internaly, serious gastric disturbances will result

Flammable, keep away from fire or flame

- use only in a well-ventilated area; fumes may be toxic

Ask a doctor before use if you have

deep or puncture woods, animal bites or serious burns.

When using this product

- do not get into eyes
- do not apply over large areas of the body
- do not use longer than one week unless directed by a doctor

Stop use and ask a doctor if

condition persists or gets worse

Keep out of reach of children.

In case of ingestion, get medical help or contact a Poison Control Center right away (1800-222-1222).

Directions

- clean affected area
- apply small amount of this product on the area 1-3 times daily
- if bandaged, let dry first
- may be covered with a sterile bandage

Other information

- store at room temperature
- does not contain, nor is intended as a substitute for grain or ethyl alcohol

Inactive ingredient

purified water

Principal Display Panel

Rubbing Alcohol 70% Isopropyl

first aid antiseptic

WARNING FLAMMABLE | Keep away from heat, spark, electrical, fire or flame

USE ONLY IN A WELL-VENTILATED AREA; FUMES MAY BE TOXIC

FL OZ (mL)

You may report serious side effects to 833-358-6431 Monday to Friday 9:00am to 7:00pm EST

TAMPER EVIDENT: DO NOT USE IF PRINTED SAFETY SEAL UNDER CAP IS BROKEN OR MISSING.

Distributed by: McKesson Corp.,

via SSSL Memphis, TN 38141

Package Label

FOSTER & THRIVE Rubbing Alcohol 70% Isopropyl